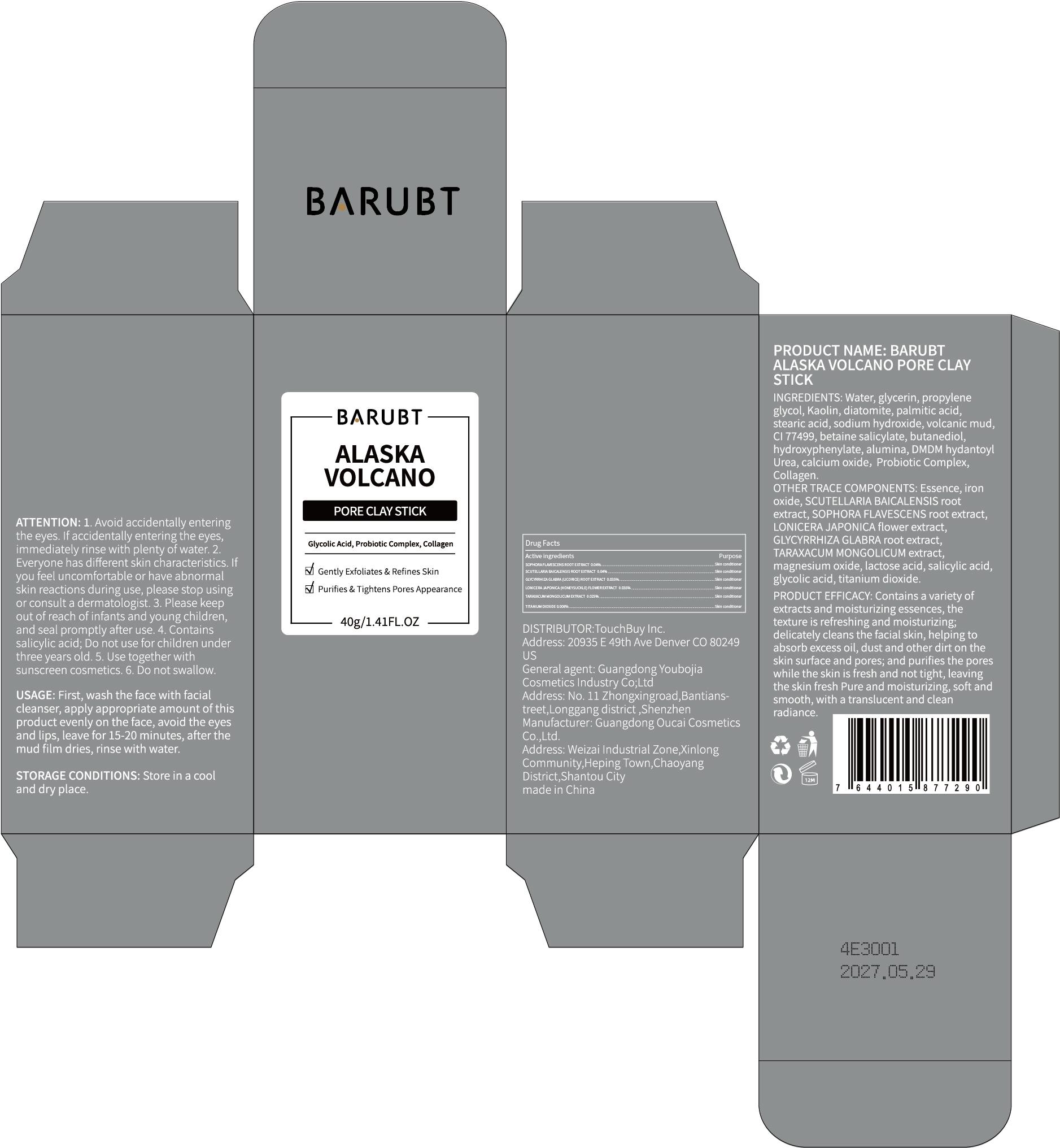 DRUG LABEL: BARUBT Alaska Volcano Pore Clay Stick
NDC: 84712-017 | Form: PASTE
Manufacturer: Guangdong Youbaijia Cosmetic Industry Co., Ltd
Category: otc | Type: HUMAN OTC DRUG LABEL
Date: 20240917

ACTIVE INGREDIENTS: TITANIUM DIOXIDE 0.0032 g/40 g; TARAXACUM MONGOLICUM 0.01 g/40 g; SCUTELLARIA BAICALENSIS ROOT 0.016 g/40 g; GLYCYRRHIZA GLABRA 0.014 g/40 g; LONICERA JAPONICA FLOWER 0.014 g/40 g; SOPHORA FLAVESCENS ROOT 0.016 g/40 g
INACTIVE INGREDIENTS: DIATOMACEOUS EARTH 4 g/40 g; KAOLIN 4 g/40 g

ACTIVE INGREDIENT

TITANIUM DIOXIDE 0.008%
SOPHORA FLAVESCENS ROOT EXTRACT 0.04%
SCUTELLARIA BAICALENSIS ROOT EXTRACT 0.04%
TARAXACUM MONGOLICUM EXTRACT 0.025%
GLYCYRRHIZA GLABRA (LICORICE) ROOT EXTRACT 0.035%
LONICERA JAPONICA (HONEYSUCKLE) FLOWER EXTRACT 0.035%

INACTIVE INGREDIENT

Water
glycerin
propylene glycol
Kaolin
diatomite
palmitic acid
stearic acid
sodium hydroxide
volcanic mud
CI 77499
betaine salicylate
butanediol
hydroxyphenylate
alumina
DMDM hydantoyl Urea
calcium oxide
Probiotic Complex
Collagen
Essence
iron oxide
magnesium oxide
lactose acid
salicylic acid
glycolic acid

Do not use on damaged skin.

Keep away from children. Do not swallow.

PURPOSE

moisturizing, cleaning

QUESTIONS

Contact name: Jessie Peng
Company phone number: +1 818 579 7288
Company e-mail: jessie@registeragentllc.com

STOP USE

lf you feel uncomfortable or have abnormal skin reactions during use, please stop using or consult a dermatologist.

WHEN USING

Avoid accidentally entering the eyes. lf accidentally entering the eyes, immediately rinse with plenty of water

WARNINGS

For external use only.

INDICATIONS AND USAGE

Contains a variety of extracts and moisturizing essences, the texture is refreshing and moisturizing;
delicately cleans the facial skin,helping to absorb excess oil, dust and other dirt on the skin surface and pores; and purifies the pores while the skin is fresh and not tight, leaving the skin fresh Pure and moisturizing, soft and smooth, with a translucent and clean radiance.

STORAGE AND HANDLING

Store in a cool and dry place,

DOSAGE AND ADMINISTRATION

First, wash the face with facial cleanser, apply appropriate amount of this product evenly on the face, avoid the eyes and lips, leave for 15-20 minutes, after the mud film dries, rinse with water.